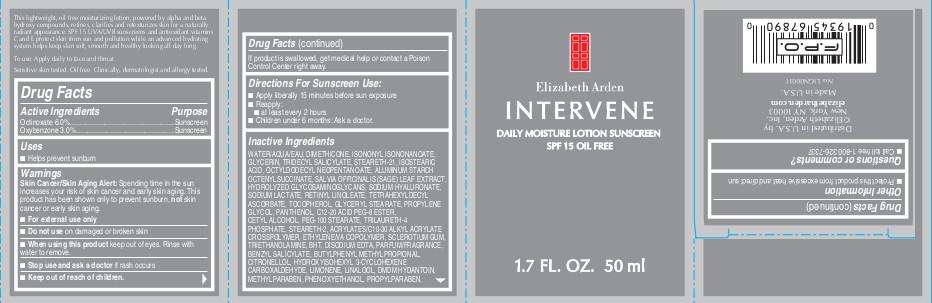 DRUG LABEL: Intervene Daily Moisture SPF 15 Oil Free
NDC: 67938-0577 | Form: LOTION
Manufacturer: Elizabeth Arden, Inc
Category: otc | Type: HUMAN OTC DRUG LABEL
Date: 20131227

ACTIVE INGREDIENTS: OCTINOXATE 3600 mg/50 mL; OXYBENZONE 1800 mg/50 mL
INACTIVE INGREDIENTS: WATER; DIMETHICONE; ISONONYL ISONONANOATE; GLYCERIN; ISOSTEARIC ACID; STEARETH-21; ALUMINUM STARCH OCTENYLSUCCINATE; OCTYLDODECYL NEOPENTANOATE; GLYCERYL STEARATE SE; PEG-100 STEARATE; CETYL ALCOHOL; PANTHENOL; SODIUM LACTATE; STEARETH-2; C12-20 ACID PEG-8 ESTER; TETRAHEXYLDECYL ASCORBATE; TRILAURETH-4 PHOSPHATE; HYDROLYZED GLYCOSAMINOGLYCANS (BOVINE; 50000 MW); DMDM HYDANTOIN; METHYLPARABEN; PROPYLENE GLYCOL; PROPYLPARABEN; TOCOPHEROL; RETINYL LINOLEATE; PHENOXYETHANOL; BUTYLPHENYL METHYLPROPIONAL; BENZYL SALICYLATE; HYDROXYISOHEXYL 3-CYCLOHEXENE CARBOXALDEHYDE

BB0577

DESCRIPTION

This lightweight, oil free moisturizing lotion, powered by alpha and beta hydroxy compounds, refines, clarifies and retexturizes skin for a naturally radiant appearance. SPF 15 UVA/UVB sunscreens and antioxidant vitamins C and E protect skin from sun and pollution while an advanced hydrating system helps keep skin soft, smooth, and healthy looking all day long. Sensitive skin tested. Oil Free. Clinically, dermatologist and allergy tested.

INDICATIONS AND USAGE

To Use: Apply daily to face and throat before sun exposure.

WARNINGS

Warning: Skin Cancer/Skin Aging Alert: Spending time in the sun increases your risk of skin cancer and early skin aging. This product has been shown to prevent sunburnm not skin cancer or early skin aging. For external us only.

OTC - ACTIVE INGREDIENT

Active Ingredients: Octinoxate 6.0% w/w, Oxybenzone 3.0% w/w.

INACTIVE INGREDIENT

Other Ingredients:

WATER/AQUA/EAU, DIMETHICONE, ISONONYL ISONONANOATE, GLYCERIN, TRIDECYL SALICYLATE, STEARETH-21, ISOSTEARIC ACID, OCTYLDODECYL NEOPENTANOATE, ALUMINUM STARCH OCTENYLSUCCINATE, SALVIA OFFICINALIS (SAGE) LEAF EXTRACT, HYDROLYZED GLYCOSAMINOGLYCANS, SODIUM HYALURONATE, SODIUM LACTATE, RETINYL LINOLEATE, TETRAHEXYLDECYL ASCORBATE, TOCOPHEROL, GLYCERYL STEARATE, PROPYLENE GLYCOL, PANTHENOL, C12-20 ACID PEG-8 ESTER, CETYL ALCOHOL, PEG-100 STEARATE, TRILAURETH-4 PHOSPHATE, STEARETH-2, ACRYLATES/C10-30 ALKYL ACRYLATE CROSSPOLYMER, ETHYLENE/VA COPOLYMER, SCLEROTIUM GUM, TRIETHANOLAMINE, BHT, DISODIUM EDTA, PARFUM/FRAGRANCE, BENZYL SALICYLATE, BUTYLPHENYL METHYLPROPIONAL, CITRONELLOL, HYDROXYISOHEXYL 3-CYCLOHEXENE CARBOXALDEHYDE, LIMONENE, LINALOOL, DMDM HYDANTOIN, METHYLPARABEN, PHENOXYETHANOL, PROPYLPARABEN.

DOSAGE & ADMINISTRATION

Apply liberally 15 minutes before sun exposure. Reapply: at least every 2 hours.

OTC - KEEP OUT OF REACH OF CHILDREN

Keep out of reach of children.

OTC - PURPOSE

SPF 15 UVA/UVB sunscreens protect skin from sun.

OTC - WHEN USING

Avoid contact with eyes.